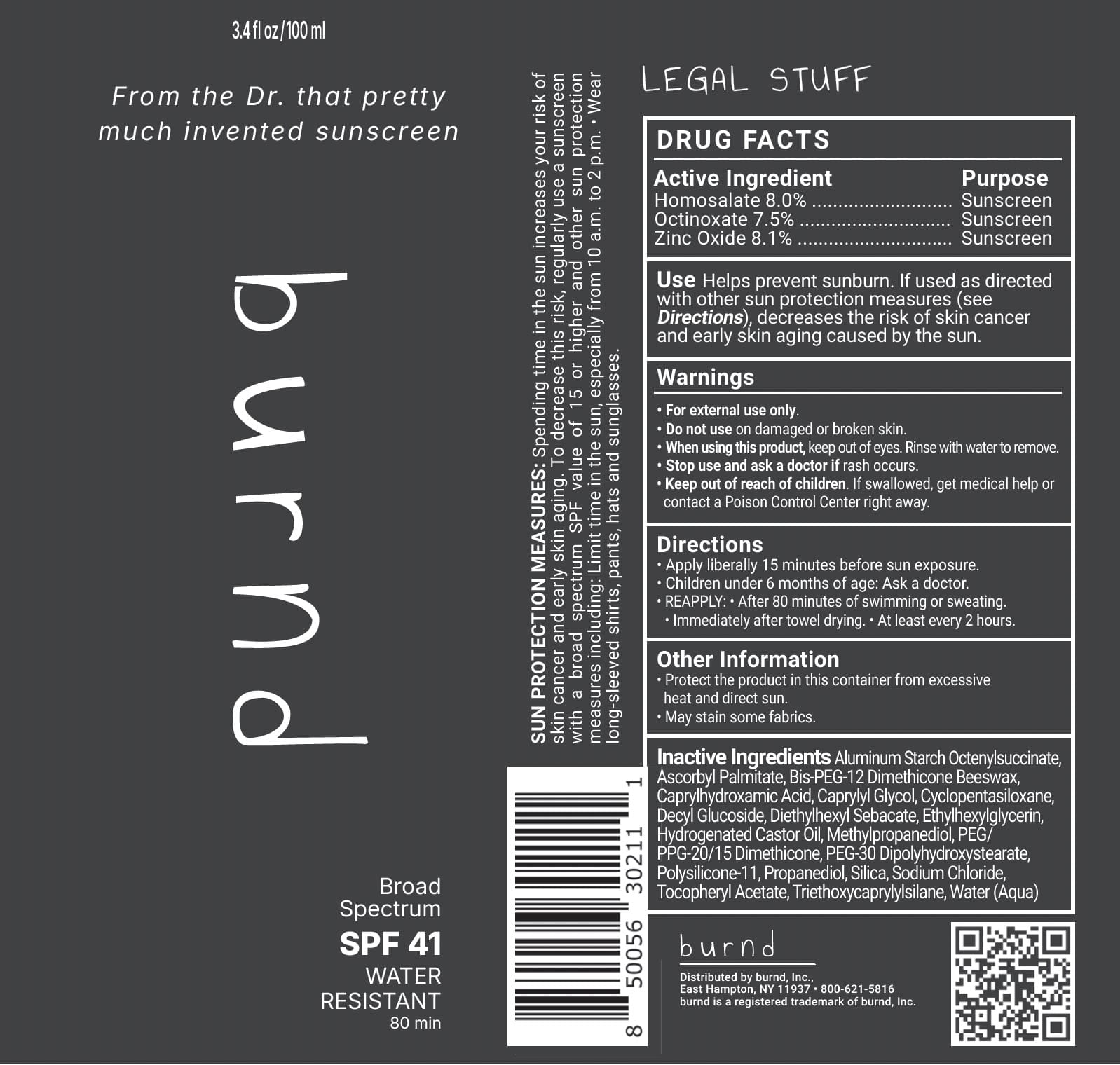 DRUG LABEL: burnd
NDC: 85455-100 | Form: LOTION
Manufacturer: BURND LLC
Category: otc | Type: HUMAN OTC DRUG LABEL
Date: 20260128

ACTIVE INGREDIENTS: HOMOSALATE 8 g/100 mL; OCTINOXATE 7.5 g/100 mL; ZINC OXIDE 8.1 g/100 mL
INACTIVE INGREDIENTS: TRIETHOXYCAPRYLYLSILANE; HYDROGENATED CASTOR OIL; WATER; DIETHYLHEXYL SEBACATE; ALUMINUM STARCH OCTENYLSUCCINATE; BIS-PEG-12 DIMETHICONE (70 MPA.S); ETHYLHEXYLGLYCERIN; SILICON DIOXIDE; SODIUM CHLORIDE; PEG-30 DIPOLYHYDROXYSTEARATE; .ALPHA.-TOCOPHEROL ACETATE; PEG/PPG-20/15 DIMETHICONE; DIMETHICONE/VINYL DIMETHICONE CROSSPOLYMER (SOFT PARTICLE); ASCORBYL PALMITATE; CAPRYLHYDROXAMIC ACID; METHYLPROPANEDIOL; CYCLOPENTASILOXANE; PROPANEDIOL; CAPRYLYL GLYCOL; DECYL GLUCOSIDE

burnd SPF 41 Sunscreen

Active Ingredients

Homosalate 8.0 %

Octinoxate 7.5%

Zinc Oxide 8.1%

Purpose

Sunscreen

Uses

- Helps prevent sunburn.
- If used as directed with other sun protection measures (see Directions),decreases the risk of skin cancer and early skin aging caused by the sun

Warnings:

• For external use only.
• Do not useon damaged or broken skin.
• When using this product, keep out of eyes. Rinse with water to remove.
• Stop use and ask a doctorif rash occurs.

Keep out of reach of children

If swallowed, get medical help or contact a Poison Control Center right away.

Directions:

Apply liberally 15 minutes before sun exposure.
• REAPPLY: • After 80 minutes of swimming or sweating.
• Immediately after towel drying. • At least every 2 hours.

SUN PROTECTION MEASURES: Spending time in the sun increases your risk ofskin cancer and early skin aging. To decrease this risk, regularly use a sunscreen with a broad spectrum SPF value of 15 or higher and other sun protection measures including:

- Limit time in the sun, especially from 10 a.m. to 2 p.m.
- Wear long-sleeved shirts, pants, hats and sunglasses.
- Children under 6 months of age: Ask a doctor.

Other Information:

- Protect the product in this container from excessive heat and direct sun.
- May stain some fabrics.

Inactive Ingredients:

Aluminum Starch Octenylsuccinate,Ascorbyl Palmitate, Bis-PEG-12 Dimethicone Beeswax,Caprylhydroxamic Acid, Caprylyl Glycol, Cyclopentasiloxane,Decyl Glucoside, Diethylhexyl Sebacate, Ethylhexylglycerin,Hydrogenated Castor Oil, Methylpropanediol, PEG/PPG-20/15 Dimethicone, PEG-30 Dipolyhydroxystearate,Polysilicone-11, Propanediol, Silica, Sodium Chloride,Tocopheryl Acetate, Triethoxycaprylylsilane, Water (Aqua)